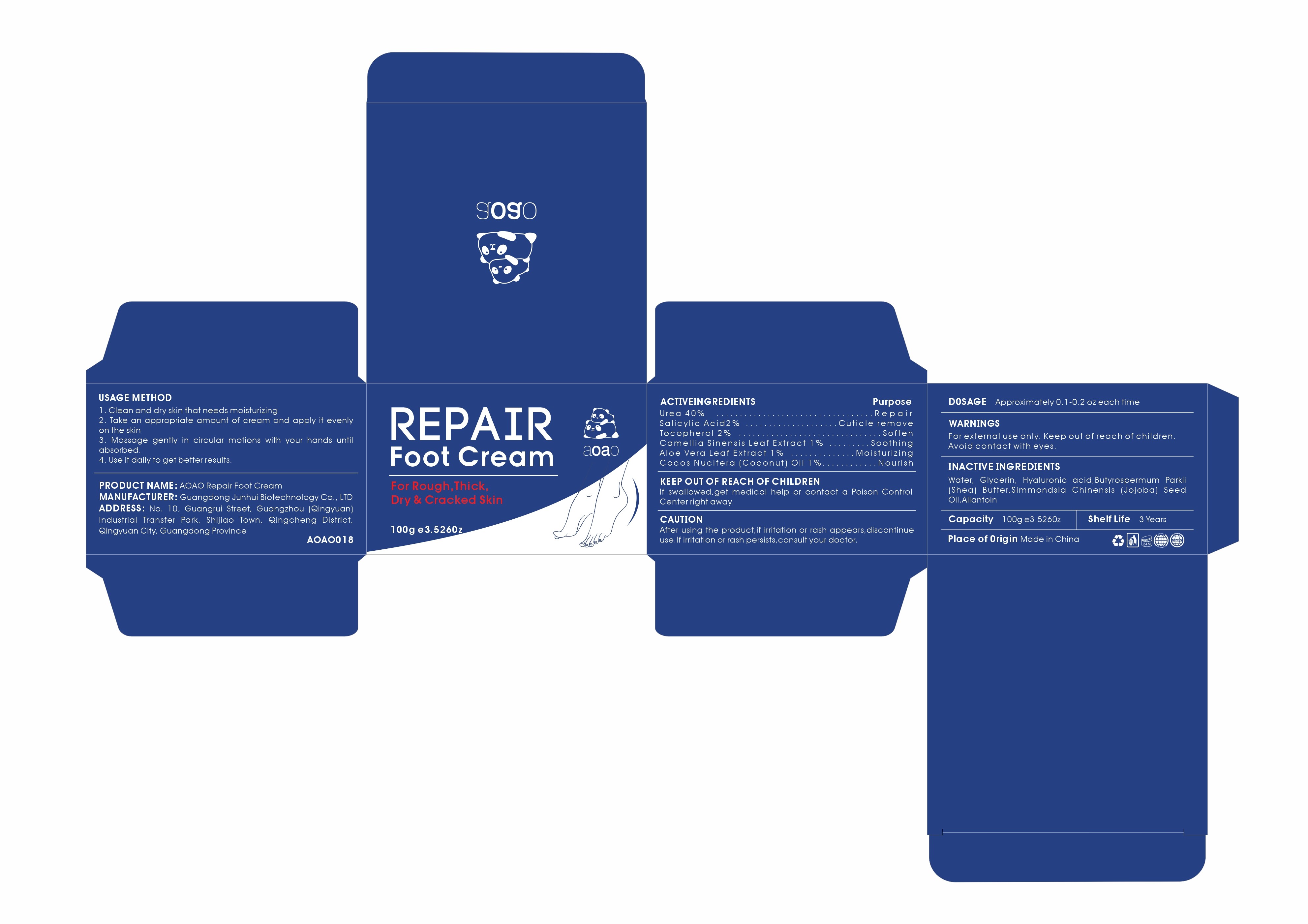 DRUG LABEL: AOAO Repair Foot Cream
NDC: 84509-010 | Form: CREAM
Manufacturer: Guangdong Junhui Biotechnology Co.,LTD
Category: otc | Type: HUMAN OTC DRUG LABEL
Date: 20250108

ACTIVE INGREDIENTS: UREA 40000 mg/100 g; TOCOPHEROL 2000 mg/100 g; SALICYLIC ACID 2000 mg/100 g; GREEN TEA LEAF 1000 mg/100 g; ALOE VERA LEAF 1000 mg/100 g; COCONUT OIL 1000 mg/100 g
INACTIVE INGREDIENTS: WATER; ALLANTOIN; SHEA BUTTER; GLYCERIN; HYALURONIC ACID; JOJOBA OIL

Active Ingredients

Urea 40%
Salicylic Acid 2%
Tocopherol 2%
Camellia Sinensis Leaf Extract 1%
Aloe Vera Leaf Extract 1%
Cocos Nucifera (Coconut) Oil 1%

Purpose

Repair
Cuticle remove
Soften
Soothing
Moisturizing
Nourish

Uses

1. Clean and dry skin that needs moisturizing
2. Take an appropriate amount of cream and apply it evenly on the skin
3. Massage gently in circular motions with your hands until absorbed.
4. Use it daily to get better results.

Warnings

For external use only. Keep out of reach of children. Avoid contact with eyes.

Keep out of reach of children

lf swallowed,get medical help or contact a Poison Control Center right away.

CAUTION

After using the product,if irritation or rash appears,discontinue use.If irritation or rash persists,consult your doctor.

D0SAGE

Approximately 0.1-0.2 ozeach time

Inactive Ingredients

Water, Glycerin, Hyaluronic acid,Butyrospermum Parkii (Shea) Butter,Simmondsia Chinensis (Jojoba) Seed Oil,Allantoin

Manufacturer

Guangdong Junhui Biotechnology Co., LTD

Address

No. 10, Guangrui Street, Guangzhou (Qingyuan) Industrial Transfer Park, Shijiao Town, Qingcheng District, Qingyuan City, Guangdong Province

Capacity

100 g e3.5260z

Shelf Life

3 Years

Place of Origin

Made in China

Product Name

AOAO Repair Foot Cream